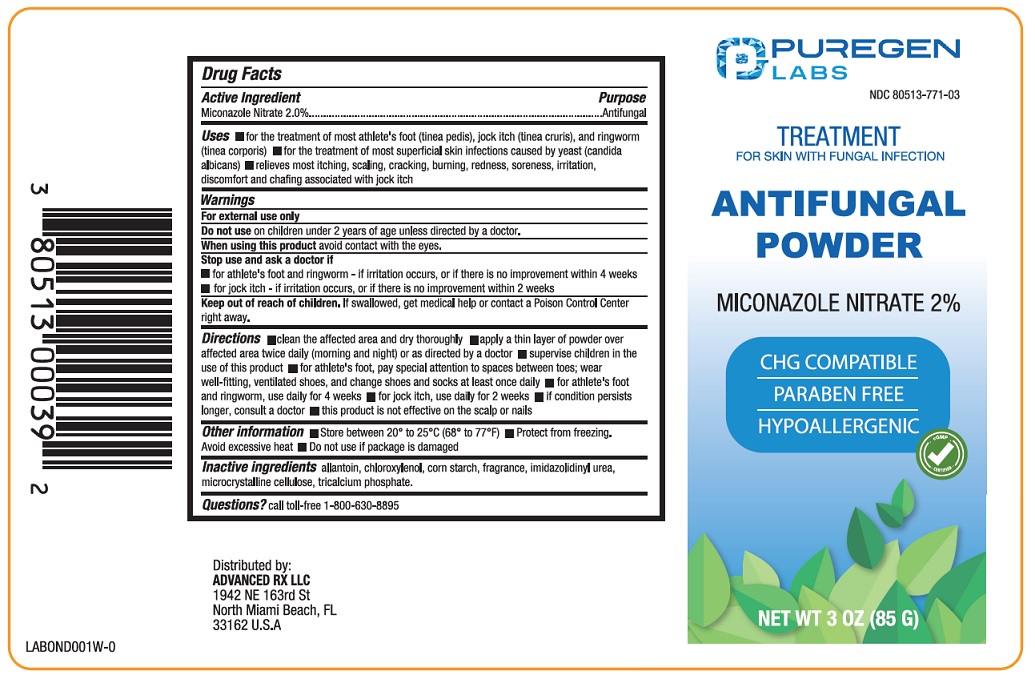 DRUG LABEL: Antifungal
NDC: 80513-771 | Form: POWDER
Manufacturer: Advanced Rx LLC
Category: otc | Type: HUMAN OTC DRUG LABEL
Date: 20250728

ACTIVE INGREDIENTS: MICONAZOLE NITRATE 20 mg/1 g
INACTIVE INGREDIENTS: ALLANTOIN; CHLOROXYLENOL; STARCH, CORN; IMIDUREA; MICROCRYSTALLINE CELLULOSE; TRICALCIUM PHOSPHATE

Active Ingredient

Miconazole Nitrate 2%

Purpose

Antifungal

Uses

- for the treatment of most athlete’s foot (tinea pedis), jock itch (tinea cruris), and ringworm (tinea corporis)
- for the treatment of most superficial skin infections caused by yeast (candida albicans)
- relieves most itching, scaling, cracking, burning, redness, soreness, irritation, discomfort and chaﬁng associated with jock itch

Warnings

For external use only.

Do not use on children under 2 years of age unless directed by a doctor.

When using this product avoid contact with the eyes.

Stop and ask a doctor if

- for athlete’s foot and ringworm - if irritation occurs, or if there is no improvement within 4 weeks
- for jock itch - if irritation occurs, or if there is no improvement within 2 weeks

Keep out of reach of children.

If swallowed, get medical help or contact a Poison Control Center right away.

Directions

- clean the affected area and dry thoroughly
- apply a thin layer of powder over affected area twice daily (morning and night) or as directed by a doctor
- supervise children in the use of this product
- for athlete's foot, pay special attention to spaces between the toes; wear well-fitting, ventilated shoes, and change shoes and socks at least once daily
- for athlete's foot and ringworm, use daily for 4 weeks; for jock itch, use daily for 2 weeks
- if conditions persist longer, consult a doctor
- this product is not effective on the scalp or nails

Other information

- Store between 20º to 25ºC (68º to 77ºF)
- Protect from freezing. Avoid excessive heat.
- Do not use if package is damaged.

Inactive ingredients

allantoin, chloroxylenol, corn starch, fragrance, imidazolidinyl urea, microcrystalline cellulose, tricalicum phosphate.

Questions?

call toll free 1-800-630-8895